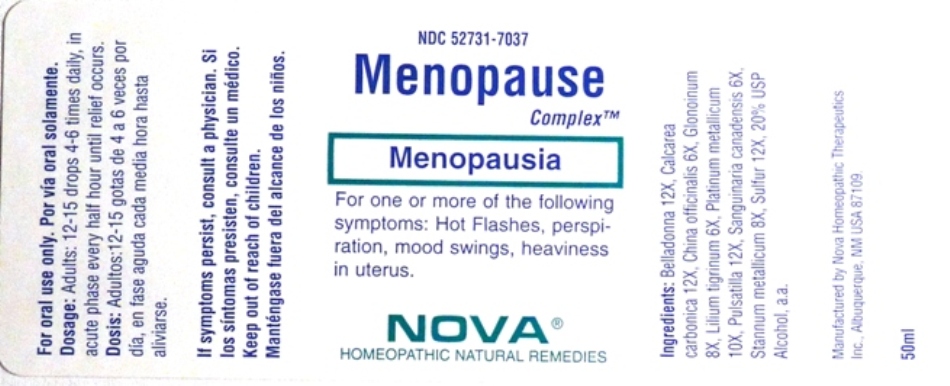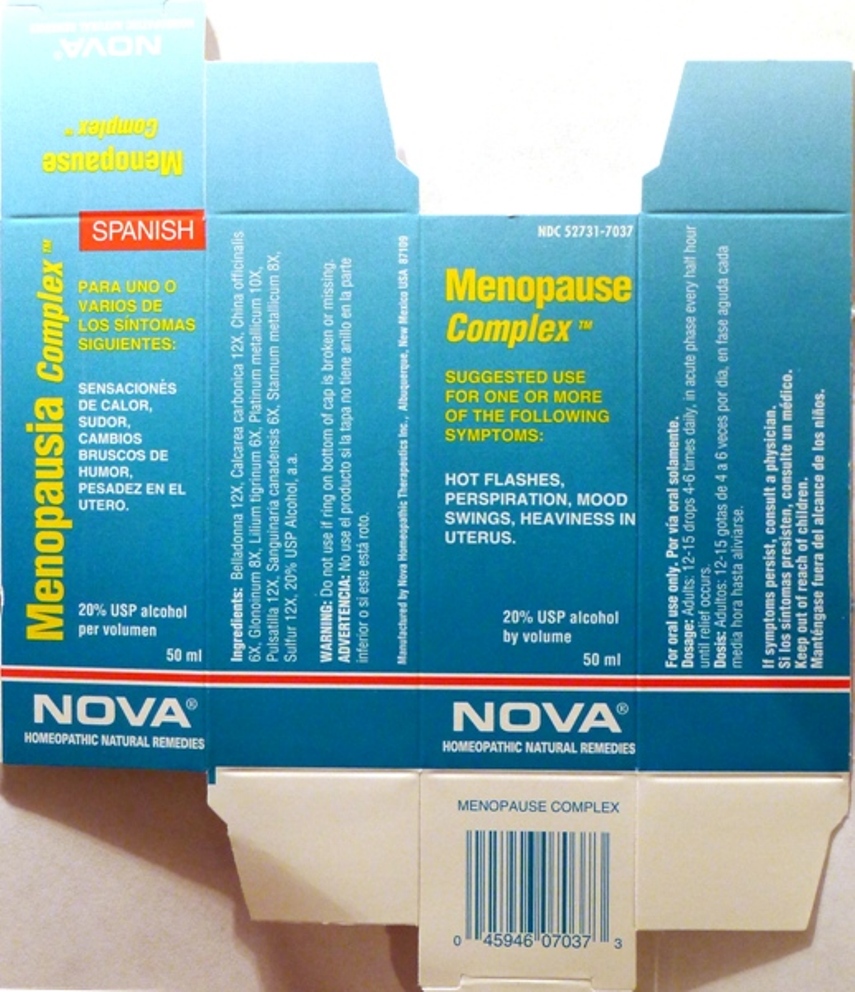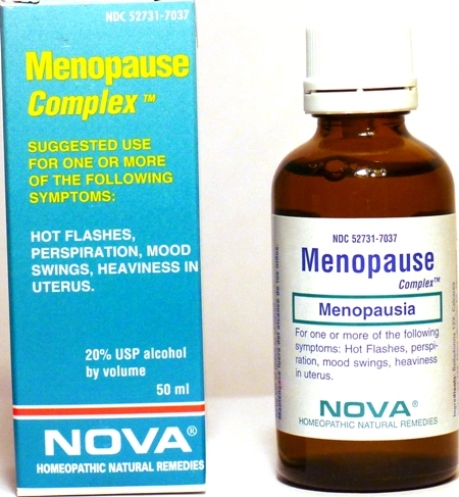 DRUG LABEL: Menopause Complex
NDC: 52731-7037 | Form: LIQUID
Manufacturer: Nova Homeopathic Therapeutics, Inc.
Category: homeopathic | Type: HUMAN OTC DRUG LABEL
Date: 20110601

ACTIVE INGREDIENTS: ATROPA BELLADONNA 12 [hp_X]/1 mL; OYSTER SHELL CALCIUM CARBONATE, CRUDE 12 [hp_X]/1 mL; CINCHONA PUBESCENS BARK 6 [hp_X]/1 mL; NITROGLYCERIN 8 [hp_X]/1 mL; LILIUM LANCIFOLIUM FLOWERING TOP 6 [hp_X]/1 mL; PLATINUM 10 [hp_X]/1 mL; PULSATILLA VULGARIS 12 [hp_X]/1 mL; SANGUINARIA CANADENSIS ROOT 6 [hp_X]/1 mL; TIN 8 [hp_X]/1 mL; SULFUR 12 [hp_X]/1 mL
INACTIVE INGREDIENTS: ALCOHOL

Menopause Complex

Purpose:

Suggested use for one or more of the following symptoms:

Hot flashes, perspiration, mood swings, heaviness in uterus.

Usage and Dosage:

For oral use only.

DOSAGE AND ADMINISTRATION

Adults:
In Acute Phase:
12-15 drops, every half hour until relief occurs
When Relief Occurs:
12-15 drops, 4-6 times per day

Warnings:

Keep out of reach of children.

WARNINGS

If symptoms persist, consult a physician.
Do not use if ring on bottom of cap is broken or missing.

Active Ingredients:

Belladonna 12X, Calcarea carbonica 12X, China officinalis 6X, Glonoinum 8X, Lilium Tigrinum 6X, Platinum metallicum 10X, Pulsatilla 12X, Sanguinaria canadensis 6X, Stannum metallicum 8X, Sulfur 12X

Inactive Ingredients:

Alcohol, 20% USP

QUESTIONS

Manufactured by Nova Homeopathic Therapeutics Inc., Albuquerque, New Mexico USA 87109
1-800-225-8094

PACKAGE LABEL

Menopause Complex Product

Menopause Complex Bottle Label

Menopause Complex Box